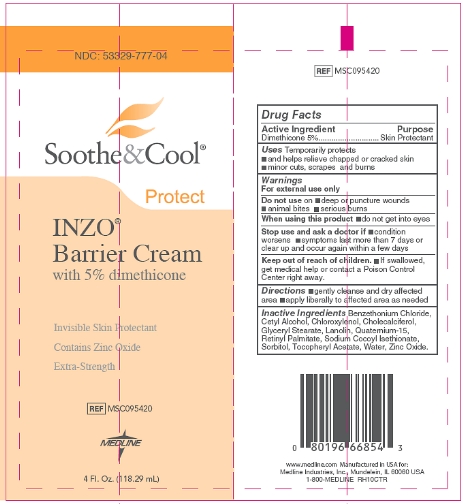 DRUG LABEL: Soothe and Cool INZO Barrier
NDC: 53329-777 | Form: CREAM
Manufacturer: Medline Industries, LP
Category: otc | Type: HUMAN OTC DRUG LABEL
Date: 20211117

ACTIVE INGREDIENTS: DIMETHICONE 5 g/100 mL
INACTIVE INGREDIENTS: BENZETHONIUM CHLORIDE; CETYL ALCOHOL; CHLOROXYLENOL; CHOLECALCIFEROL; GLYCERYL MONOSTEARATE; LANOLIN; QUATERNIUM-15; VITAMIN A PALMITATE; SORBITOL; .ALPHA.-TOCOPHEROL ACETATE, D-; WATER; ZINC OXIDE

777 Soothe and Cool INZO Barrier

Active ingredient

Dimethicone 5%

Purpose

Skin Protectant

Uses

Temporarily protects

- and helps relieve chapped or cracked skin
- minor cuts, scrapes, and burns

Warnings

For external use only

Do not use

on

- deep or puncture wounds
- animal bites
- serious burns

When using this product

- do not get into eyes

Stop use and ask a doctor if

- condition worsens
- symptoms last more than 7 days or clear up and occur again within a few days

Keep out of reach of children.

If swallowed get medical help or contact a Poison Control Center right away.

Directions

- gently cleanse and dry affected area
- apply liberally to affected area as needed

Inactive ingredients

Benzethonium Chloride, Cetyl Alcohol, Chloroxylenol, Cholecalciferol, Glyceryl Stearate, Lanolin, Quaternium-15, Retinyl Palmitate, Sodium Cocoyl Isethionate, Sorbitol, Tocopheryl Acetate, Water, Zinc Oxide.

Package/Label Principal Display Panel

NDC: 53329-777-04

Soothe & Cool

Protect

INZO Barrier Cream

with 5% dimethicone
Invisible Skin Protectant

Contains Zinc Oxide

Extra-Strength

REF MSC095420

Medline

4 Fl. Oz. (118.29 mL)